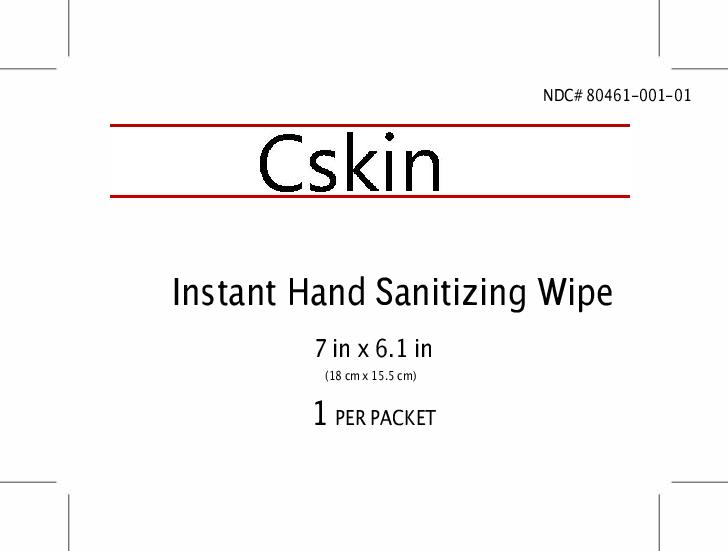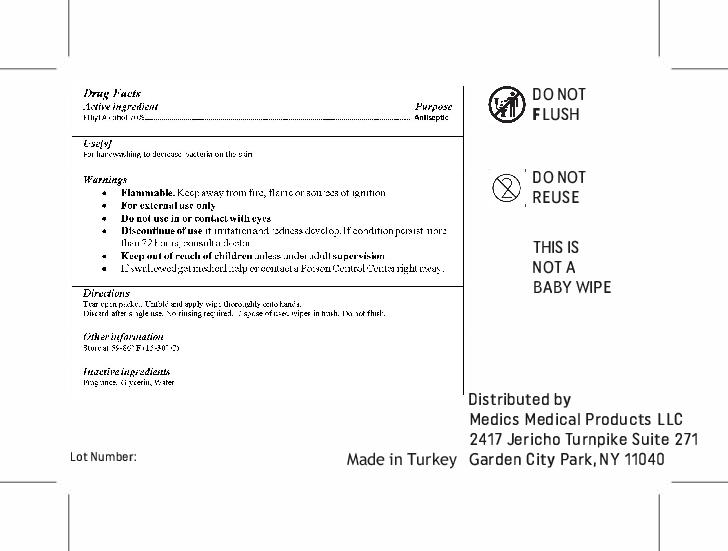 DRUG LABEL: Cskin Hand Sanitizing Wipe
NDC: 80461-001 | Form: SOLUTION
Manufacturer: Medics Medical Products LLC
Category: otc | Type: HUMAN OTC DRUG LABEL
Date: 20201221

ACTIVE INGREDIENTS: ALCOHOL 0.75 mL/1 mL
INACTIVE INGREDIENTS: GLYCERIN; WATER

Cskin Instant Hand Sanitizing Wipe

Active Ingredient(s)

Ethyl Alcohol 70%

Purpose: Antiseptic

Purpose

Antiseptic, Hand Sanitizer

Use

Hand Sanitizer to help reduce bacteria that potentially can cause disease.

Warnings

For external use only. Flammable. Keep away from fire, flame, or sources of ignition.

Do not use

in or contact with eyes.

Keep out of reach of children, unless under adult supervision. If swallowed, get medical help or contact a Poison Control Center right away.

STOP USE

Discontinue use if irritation and redness develops. If condition persists more than 72 hours, cosult a doctor.

Keep out of reach of children. If swallowed, get medical help or contact a Poison Control Center right away.

Directions

- Tear open packet. Unfold and apply wipe thoroughly onto hands.
- Discard after single use. Discard after single use. No rinsing required.Dispose of used wipes in the trash.
- Do not flush.

Other information

- Store between 15-30C (59-86F)

Inactive ingredients

fragrance, glycerin, purified water

Package Label - Principal Display Panel

NDC: 80461-001-01